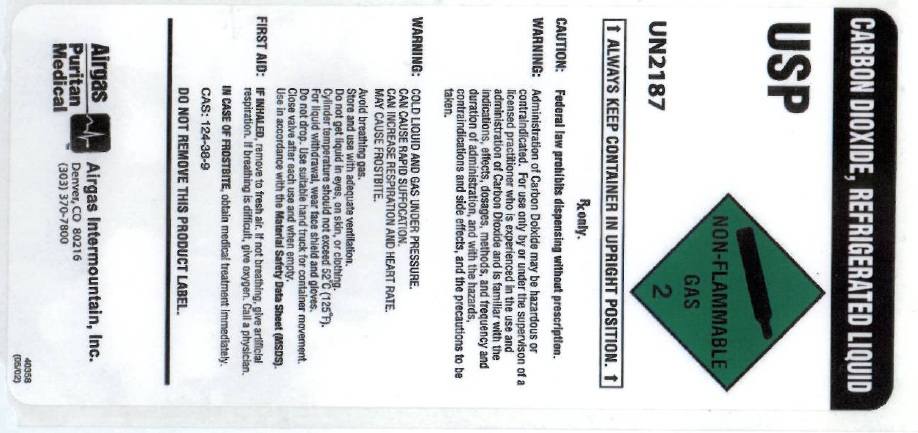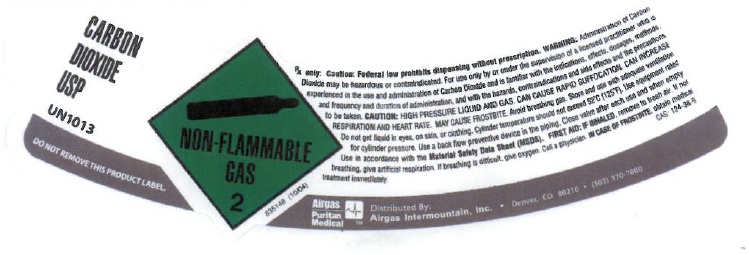 DRUG LABEL: Carbon Dioxide
NDC: 58420-006 | Form: GAS
Manufacturer: Airgas Intermountain Inc
Category: prescription | Type: HUMAN PRESCRIPTION DRUG LABEL
Date: 20100622

ACTIVE INGREDIENTS: Carbon Dioxide 992 mL/1 L

carbon dioxide

PACKAGE LABEL

CARBON DIOXIDE, REFRIGERATED LIQUID USP
UN2187
NON-FLAMMABLE 2
ALWAYS KEEP CONTAINER IN UPRIGHT POSITION
Rx only. CAUTION: Federal law prohibits dispensing without a prescription. WARNING: Administration of Carbon Dioxide may be hazardous or contraindicated. For use only by or under the supervision of a licensed practitioner who is experienced in the use and administration of Carbon Dioxide, and is familiar with the indications, effects, dosages, methods, and frequency and duration of administration, and with the hazards, contraindications and side effects, and the precautions to be taken.
CAUTION: COLD LIQUID AND GAS UNDER PRESSURE. CAN CAUSE RAPID SUFFOCATION. CAN INCREASE RESPIRATION AND HEART RATE. MAY CAUSE FROSTBITE. Avoid breathing gas. Store and use with adequate ventilation. Do not get liquid in eyes, on skin, or clothing. Cylinder temperature should not exceed 52oC(125oF). For liquid withdrawal, wear face shield and gloves. Do not drop. Use suitable hand truck for container movement. Close valve after each use and when empty. Use in accordance with the Material Safety Data Sheet (MSDS).
FIRST AID: IF INHALED, remove to fresh air. If not breathing, give artificial respiration. If breathing is difficult, give oxygen. Call a physician. IN CASE OF FROSTBITE, obtain medical treatment immediately. CAS: 124-38-9
DO NOT REMOVE THIS PRODUCT LABEL.
AIRGAS PURITAN MEDICAL Distributed By: Airgas Intermountain, Inc. Denver, CO 80216 (303) 370-7800
40358 (05/02)

PACKAGE LABEL

CARBON DIOXIDE USP
UN1013
DO NOT REMOVE THIS PRODUCT LABEL
NON-FLAMMABLE 2
838148 (10/04)
Rx only. CAUTION: Federal law prohibits dispensing without a prescription. WARNING: Administration of Carbon Dioxide may be hazardous or contraindicated. For use only by or under the supervision of a licensed practitioner who is experienced in the use and administration of Carbon Dioxide, and is familiar with the indications, effects, dosages, methods, and frequency and duration of administration, and with the hazards, contraindications and side effects, and the precautions to be taken.
CAUTION: HIGH PRESSURE LIQUID AND GAS. CAN CAUSE RAPID SUFFOCATION. CAN INCREASE RESPIRATION AND HEART RATE. MAY CAUSE FROSTBITE. Avoid breathing gas. Store and use with adequate ventilation. Do not get liquid in eyes, on skin, or clothing. Cylinder temperature should not exceed 52oC(125oF). Use equipment rated for cylinder pressure. Use a back flow preventive device in the piping. Close valve after each use and when empty. Use in accordance with the Material Safety Data Sheet (MSDS).
FIRST AID: IF INHALED, remove to fresh air. If not breathing, give artificial respiration. If breathing is difficult, give oxygen. Call a physician. IN CASE OF FROSTBITE, obtain medical treatment immediately. CAS: 124-38-9
AIRGAS PURITAN MEDICAL Distributed By: Airgas Intermountain, Inc. Denver, CO 80216 (303) 370-7800